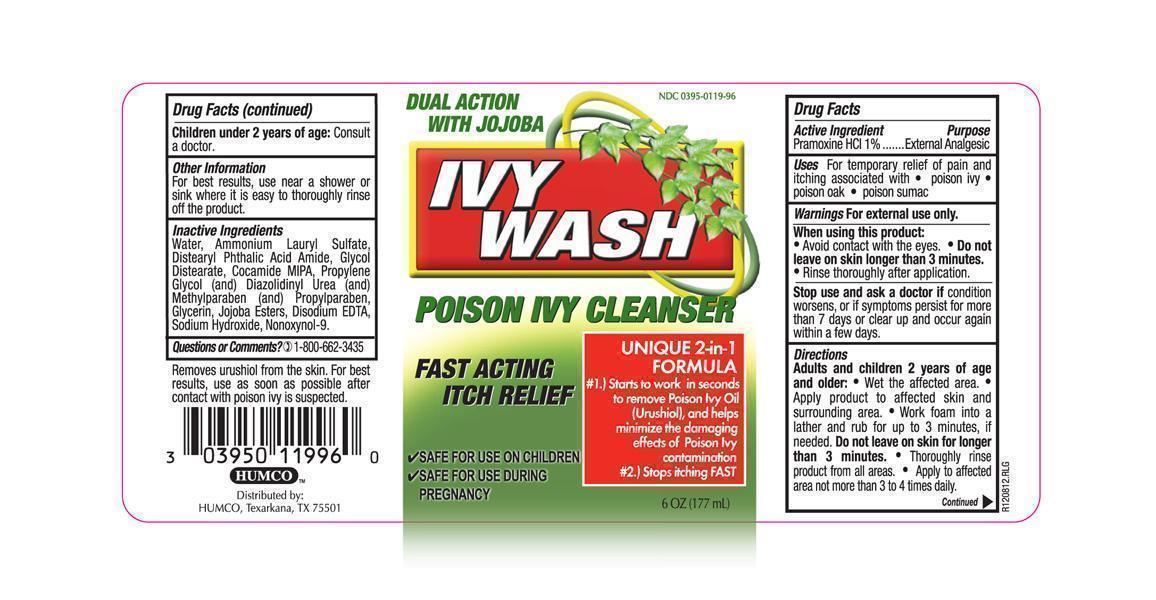 DRUG LABEL: Ivy Wash
NDC: 0395-0119 | Form: LOTION
Manufacturer: Humco Holding Group, Inc.
Category: otc | Type: HUMAN OTC DRUG LABEL
Date: 20171214

ACTIVE INGREDIENTS: PRAMOXINE HYDROCHLORIDE 10 1/1 mL
INACTIVE INGREDIENTS: WATER; AMMONIUM LAURYL SULFATE; GLYCOL DISTEARATE; PROPYLENE GLYCOL; DIAZOLIDINYL UREA; METHYLPARABEN; PROPYLPARABEN; GLYCERIN; HYDROLYZED JOJOBA ESTERS (ACID FORM); EDETATE DISODIUM; SODIUM HYDROXIDE; NONOXYNOL-9

Ivy Wash

Drug Facts

active ingredient

Pramoxine HCl 1%

Purpose

External analgesic

Uses

For temporary relief of pain and itching associated with poison ivy, poison oak, poison summac

Warnings

For external use only

When using this product

Avoid contact with the eyes. Do not leave on skin longer than three minutes. rinse throughly after application.

Stop use and ask a doctor if

conditions worsens or if symptoms persist for more than 7 days or clear up and occur again within a few days.

Directions

Adult and children 2 years of age and older. Wet affected areas. Apply the product to affected skin and surrounding area. work foam into a lather and rub for up to 3 minutes, if needed. Do not leave on skin for longer than 3 minutes. throughly rinse product from all areas. Apply to affected area not more than 3 to 4 times daily. Children under 2 years of age. Consult a doictor.

Other Information

For best results, use near a shower or sink where it is easy to throughly rinse off product.

Inactive Ingredients

Water, Ammonium Laurl Sulfate, Distearyl Phtalic Acid Amide, Glycol Distearate, Cocamide MIPA, Propylene Glycol, (and) Diazodinyl Urea (and) Methylparaben (and) Propylparaben, Glycerin, Jojoba Esters, Disodium EDTA, Sodium Hydroxide, Nonoxynol-9.

Questions or Comments?

1-800-662-3435

Removes urishiol from the skin. For best results, use as soon as possible after contact with poisson ivy is suspected.

Principal display panel

Dual Action with Jojoba. NDC 0395-0119-96. IVY WASH. POISON IVY CLEANER. FAST ACTING ITCH RELIEF. SAFE FOR USE IN CHILDREN. SAFE FOR USE DURING PREGNACY. UNIQUE 2-IN-1 FORMULA. #1) Starts to work in seconds to remove Poison Ivy Oil (Urishiol), and helps minimize the damaging effects of Poison Ivy contamination. #2) Stops itching FAST. 6OZ (177 mL).